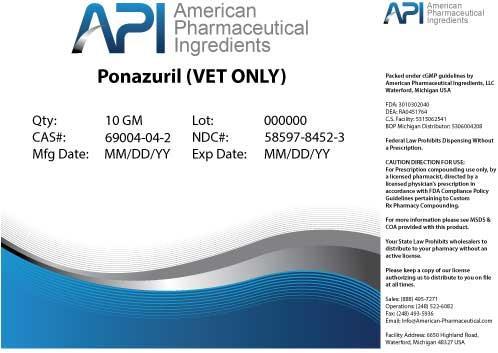 DRUG LABEL: Ponazuril
NDC: 58597-8452 | Form: POWDER
Manufacturer: AMERICAN PHARMACEUTICAL INGREDIENTS LLC
Category: other | Type: BULK INGREDIENT
Date: 20140429

ACTIVE INGREDIENTS: Ponazuril 1 g/1 g

Ponazuril